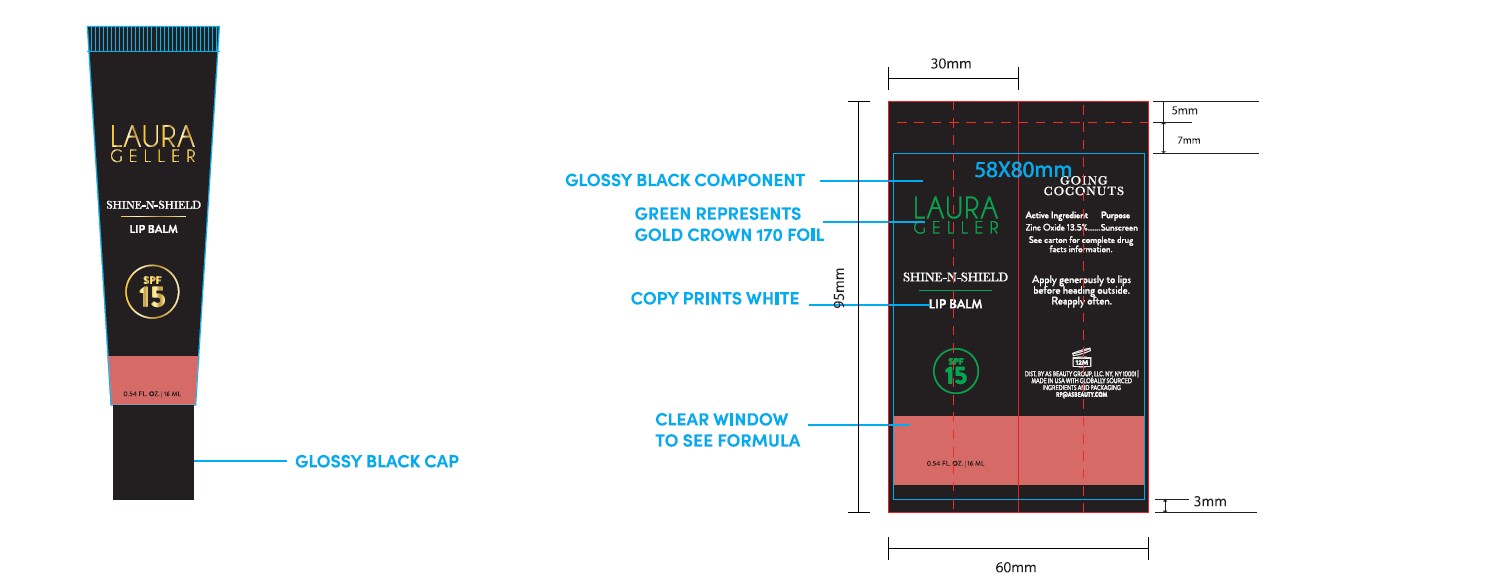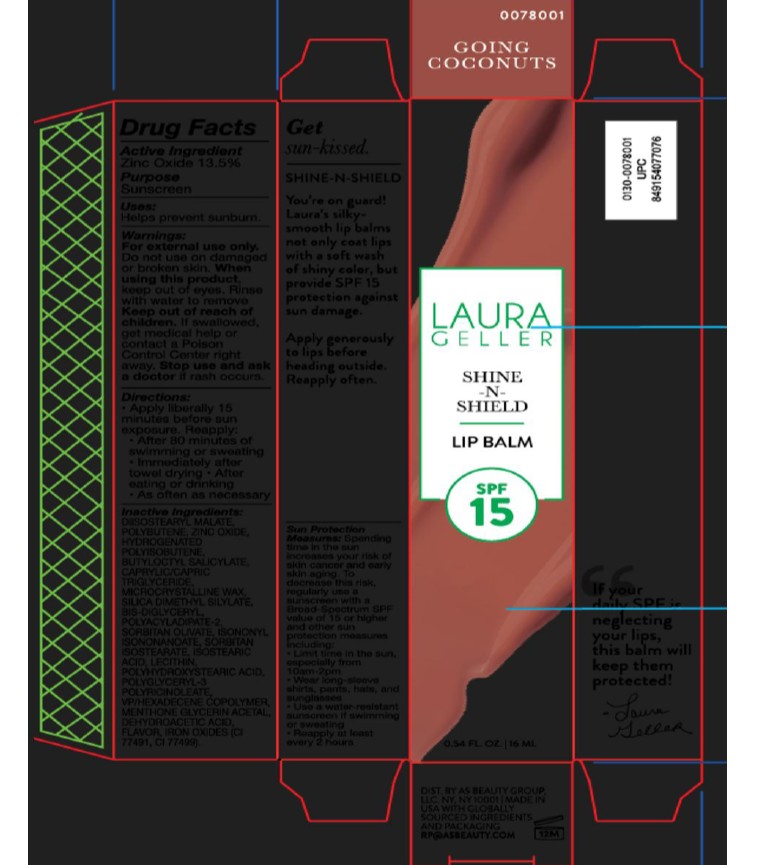 DRUG LABEL: LAURA GELLER X BLISS SHINE - N - SHIELD LIP BALM SPF 15 GOING COCONUTS
NDC: 68577-237 | Form: LIPSTICK
Manufacturer: COSMAX USA, CORP
Category: otc | Type: HUMAN OTC DRUG LABEL
Date: 20260301

ACTIVE INGREDIENTS: ZINC OXIDE 13.5 mg/100 mL
INACTIVE INGREDIENTS: LECITHIN, SUNFLOWER; POLYHYDROXYSTEARIC ACID (2300 MW); MICROCRYSTALLINE WAX; DIISOSTEARYL MALATE; SORBITAN ISOSTEARATE; SORBITAN OLIVATE; DEHYDROACETIC ACID; FERROUS OXIDE; CAPRYLIC/CAPRIC TRIGLYCERIDE; POLYBUTENE (1400 MW); BIS-DIGLYCERYL POLYACYLADIPATE-2; ISOSTEARIC ACID; BUTYLOCTYL SALICYLATE; POLYGLYCERYL-3 PENTARICINOLEATE; HYDROGENATED POLYISOBUTENE (1300 MW); SILICA DIMETHYL SILYLATE; MENTHONE GLYCERIN ACETAL; ISONONYL ISONONANOATE; VP/HEXADECENE COPOLYMER

LAURA GELLER SHINE-N-SHIELD LIP BALM SPF 15- GOING COCONUT

Active ingredient

Zinc Oxide 13.5%

Purpose

Sunscreen

USES

Helps prevent sunburn

Warnings:

For external use only.

Do not useon damaged or broken skin.

When using this product,keep out of eyes. rinse with water to remove

Keep out of reach of children. If swallowed, get medical help or contact a Poison Control Center right away.

Stop use and ask a doctorif rash occurs.

DIRECTIONS

- Apply liberally 15 minutes before sun exposure. Reapply:
- After 80 minutes of swimming or sweating
- Immediately after towel drying
- After eating or drinking
- As often as necessary

INACTIVE INGREDIENT

INACTIVE INGREDIENTS: DIISOSTEARYL MALATE, POLYBUTENE, HYDROGENATED POLYISOBUTENE, BUTYLOCTYL SALICYLATE, CAPRYLIC/CAPRIC TRIGLYCERIDE, MICROCRYSTALLINE WAX, SILICA DIMETHYL SILYLATE, BIS-DIGLYCERYL POLYACYLADIPATE-2, SORBITAN OLIVATE, ISONONYL ISONONANOATE, SORBITAN ISOSTEARATE, ISOSTEARIC ACID, LECITHIN, POLYHYDROXYSTEARIC ACID, POLYGLYCERYL-3 POLYRICINOLEATE, VP/HEXADECENE COPOLYMER, MENTHONE GLYCERIN ACETAL, DEHYDROACETIC ACID, FLAVOR, IRON OXIDES (CI 77491, CI 77492).

PACKAGE LABEL

Laura Geller Shine-n-Shield Lip Balm SPF 15 0.54 fl.oz./16ML